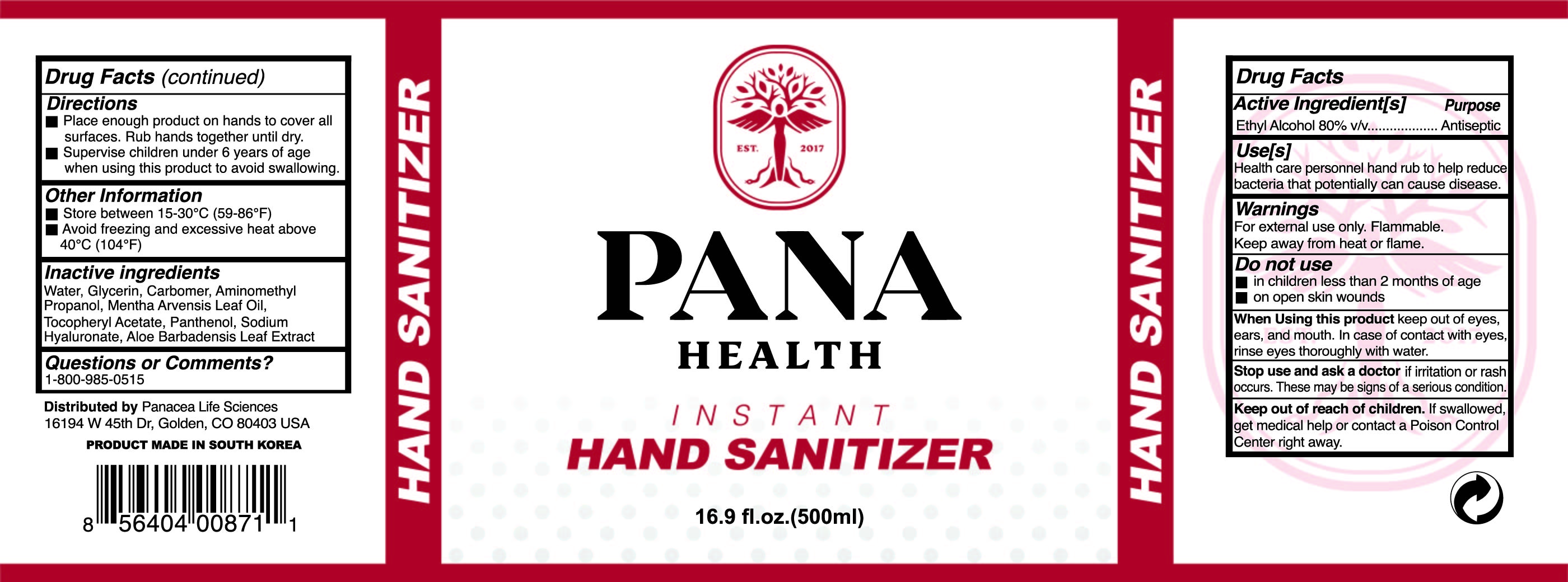 DRUG LABEL: PANA Health Instant Hand Sanitizer Gel
NDC: 73862-204 | Form: GEL
Manufacturer: E.CIS COSMETIC.Co.,Ltd
Category: otc | Type: HUMAN OTC DRUG LABEL
Date: 20200526

ACTIVE INGREDIENTS: ALCOHOL 80 mL/100 mL
INACTIVE INGREDIENTS: AMINOMETHYLPROPANOL; WATER; HYALURONATE SODIUM; GLYCERIN; CARBOMER 940; MENTHA ARVENSIS LEAF OIL; .ALPHA.-TOCOPHEROL ACETATE; PANTHENOL; ALOE VERA LEAF

PANA Health Instant Hand Sanitizer Gel

Active Ingredient(s)

Ethyl Alcohol 80% v/v..........................Antiseptic

Purpose

Purpose.Antiseptic

Use

Health care personnel hand rub to help reduce bacteria that potentially can cause disease.

Warnings

For external use only. Flammable. Keep away from heat or flame.

Do not use

■ in children less than 2 months of age

■ on open skin wounds

When using this product keep out of eyes, ears, and mouth. In case of contact with eyes, rinse eyes thoroughly with water.

Stop use and ask a doctor if irritation or rash occurs. These may be signs of a serious condition.

Keep out of reach of children. If swallowed, get medical help or contact a Poison Control Center right away.

Directions

■ Place enough product on hands to cover all surfaces. Rub hands together until dry.
■ Supervise children under 6 years of age

Other information

■ Store between 15-30°C (59-86°F)
■ Avoid freezing and excessive heat above 40°C (104°F)

Inactive ingredients

Water, Glycerin, Carbomer, Aminomethyl Propanol, Mentha Arvensis Leaf Oil, Tocopheryl Acetate, Panthenol, Sodium Hyaluronate, Aloe Barbadensis Leaf Extract

Package Label - Principal Display Panel

PANA

HEALTH

INSTANT

HAND SANITIZER

16.9 fl.oz.(500ml)